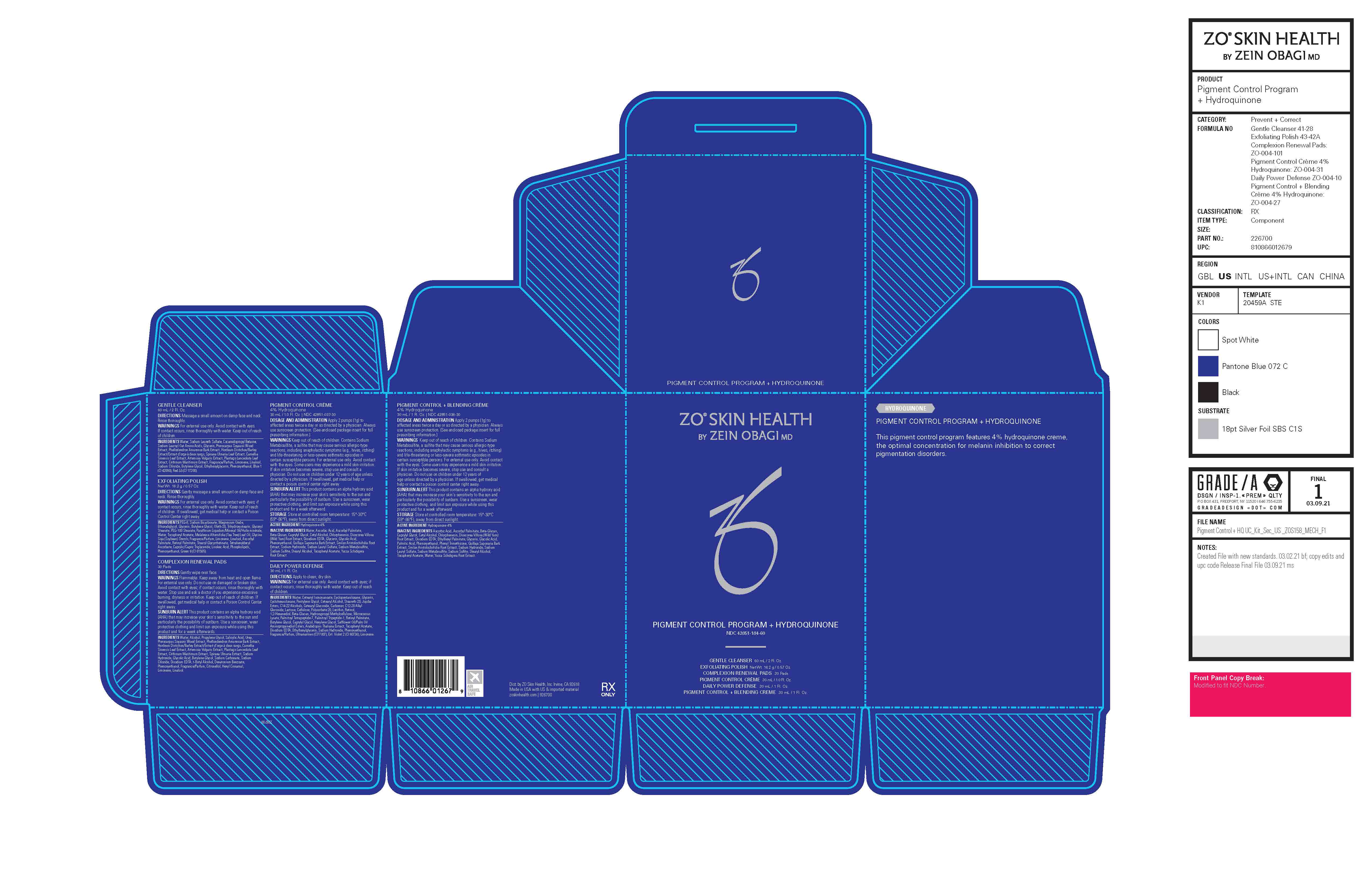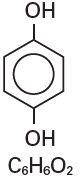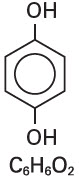 DRUG LABEL: ZO Skin Health Pigment Control Program Plus Hydroquinone
NDC: 42851-184 | Form: KIT | Route: TOPICAL
Manufacturer: ZO Skin Health, Inc.
Category: prescription | Type: HUMAN PRESCRIPTION DRUG LABEL
Date: 20241217

ACTIVE INGREDIENTS: HYDROQUINONE 40 mg/1 mL; HYDROQUINONE 0.04 g/1 mL
INACTIVE INGREDIENTS: WATER; ASCORBIC ACID; ASCORBYL PALMITATE; CAPRYLYL GLYCOL; CETYL ALCOHOL; CHLORPHENESIN; DIOSCOREA VILLOSA TUBER; EDETATE DISODIUM ANHYDROUS; GLYCERIN; GLYCOLIC ACID; PHENOXYETHANOL; QUILLAJA SAPONARIA BARK; SMILAX ARISTOLOCHIIFOLIA ROOT; SODIUM HYDROXIDE; SODIUM LAURYL SULFATE; SODIUM METABISULFITE; SODIUM SULFITE; STEARYL ALCOHOL; .ALPHA.-TOCOPHEROL ACETATE; YUCCA SCHIDIGERA ROOT; ASCORBIC ACID; ASCORBYL PALMITATE; CAPRYLYL GLYCOL; CETYL ALCOHOL; CHLORPHENESIN; DIOSCOREA VILLOSA TUBER; EDETATE DISODIUM ANHYDROUS; ETHYLHEXYL PALMITATE; GLYCERIN; GLYCOLIC ACID; PALMITIC ACID; PHENOXYETHANOL; PHENYL TRIMETHICONE; QUILLAJA SAPONARIA BARK; SMILAX ARISTOLOCHIIFOLIA ROOT; SODIUM HYDROXIDE; SODIUM LAURYL SULFATE; SODIUM METABISULFITE; SODIUM SULFITE; STEARYL ALCOHOL; .ALPHA.-TOCOPHEROL ACETATE, DL-; WATER; YUCCA SCHIDIGERA ROOT

Pigment Control Program + Hydroquinone
(Hydroquinone USP, 4%)
NDC 42851-184-60

PIGMENT CONTROL CREME

(Hydroquinone USP, 4%)

RX ONLY
FOR EXTERNAL USE ONLY:
NOT FOR OPHTHALMIC USE

DESCRIPTION

Hydroquinone is 1,4-benzendiol, with a chemical formula of C6H6O2 and a molecular weight of 110.11.

The structural formula is:

Each gram of Pigment Control Creme (Hydroquinone USP, 4%) contains Hydroquinone USP 40 mg/gm in a base of Purified Water, Ascorbic Acid, Ascorbyl Palmitate, Beta-Glucan, Caprylyl Glycol, Cetyl Alcohol, Chlorphenesin, Dioscorea Villosa (Wild Yam) Root Extract, Disodium EDTA, Glycerin, Glycolic Acid, Phenoxyethanol, Quillaja Saponaria Bark Extract, Smilax Aristolochiifolia Root Extract, Sodium Hydroxide, Sodium Lauryl Sulfate, Sodium Metabisulfite, Sodium Sulfite, Stearyl Alcohol, Tocopheryl Acetate, Yucca Schidigera Root Extract.

CLINICAL PHARMACOLOGY

Topical application of hydroquinone produces a reversible depigmentation of the skin by inhibition of the enzymatic oxidation of tyrosine to 3,4-dihydroxyphenylalanine (DOPA) and suppression of other melanocyte metabolic processes. Exposure to sunlight or ultraviolet light will cause re-pigmentation of bleached areas, which may be prevented by the use of the sunscreen agents.

INDICATIONS AND USAGE

Pigment Control Creme is indicated in the gradual bleaching of hyperpigmentation, skin conditions such as chloasma, melasma, freckles, senile lentigines, and other unwanted areas of melanin hyperpigmentation.

CONTRAINDICATIONS

Prior history of sensitivity or allergic reaction to this product or any of its ingredients. The safety of topical Hydroquinone use during pregnancy or in children (12 years and under) has not been established.

WARNINGS

Hydroquinone is a skin bleaching agent which may produce undesired effects if not used as directed. The physician should be familiar with the contents of this insert before prescribing or dispensing this product.

Contains sodium metabisulfite, a sulfite that may cause allergic-type reactions including anaphylactic symptoms and life-threatening or less severe asthmatic episodes in certain susceptible people. The overall prevalence of sulfite sensitivity in the general population is unknown and probably low. Sulfite sensitivity is seen more frequently in asthmatic than in non-asthmatic people.

Avoid unnecessary sun exposure, use an effective broad-spectrum sunscreen agent or protective clothing should be worn to cover bleached skin to prevent re-pigmentation from occurring.

Hydroquinone may produce exogenous ochronosis, a gradual blue-black darkening of the skin. If this condition occurs, discontinue treatment and consult your physician.

Avoid contact with eyes and mucous membranes. Keep out of reach of children. In case of accidental ingestion, call a physician or a poison control center immediately.

PRECAUTIONS

Test for skin sensitivity before using by applying a small amount to an unbroken patch of skin; check within 24 hours. Minor redness is not a contraindication, but where there is itching or vesicle formation or excessive inflammatory response, further treatment is not advised. Close patient supervision is recommended.

Drug Interactions

Patients are cautioned on concomitant use of medications that are known to be photosensitizing.

Carcinogenesis, Mutagenesis, Impairment of Fertility

Studies of hydroquinone in animals have demonstrated some evidence of carcinogenicity. The carcinogenic potential of hydroquinone in humans is unknown.

Pregnancy Category C

Animal reproduction studies have not been conducted with topical hydroquinone. It is also not known whether topical hydroquinone can cause fetal harm when administered to a pregnant woman or can affect reproduction capacity. Topical hydroquinone should be given to a pregnant woman only if clearly needed.

Nursing Mothers

It is not known whether this drug is excreted in human milk. Because many drugs are excreted in human milk, caution should be exercised when topical hydroquinone is administered to a nursing woman.

Pediatric Use

Safety and effectiveness for pediatric patients below the age of 12 years have not been established.

Adverse Reactions

The following reactions have been reported: dryness and fissuring of paranasal and infraorbital areas, erythema, and stinging. Occasional hypersensitivity (localized contact dermatitis) may develop. If this occurs, the medication should be discontinued, and the physician notified immediately.

Overdosage

There have been no system reactions reported from the use of topical hydroquinone. However, treatment should be limited to relatively small areas of the body at one time, since some patients experience a transient skin reddening and a mild burning sensation which does not preclude treatment.

DRUG DOSAGE AND ADMINISTRATION

A thin layer of Pigment Control Creme (Hydroquinone USP, 4%) should be applied to the affected area twice daily or as directed by a physician. If no improvement is seen after 8-12 weeks of treatment, use of this product should be discontinued. There is no recommended dosage for pediatric patients under 12 years of age except under the advice and supervision of a physician.

HOW SUPPLIED

Pigment Control Creme (Hydroquinone USP, 4%) is available as follows:

2.7 Fl. Oz. (80 mL) Bottle / NDC 42851-037-80

1.0 fl oz/30 ml Bottle / NDC 42851-037-30

STORAGE

Store at controlled room temperature: 15°-30°C (59°-86°F)

PIGMENT CONTROL + BLENDING CREME
(Hydroquinone USP, 4%)

RX ONLY
FOR EXTERNAL USE ONLY:
NOT FOR OPHTHALMIC USE

DESCRIPTION

Hydroquinone is 1,4-benzendiol, with a chemical formula of C6H6O2 and a molecular weight of 110.11.

The structural formula is:

Each gram of Pigment Control + Blending Creme contains Hydroquinone USP 40mg/gm in a base of Ascorbic Acid, Ascorbyl Palmitate, Beta-Glucan, Caprylyl Glycol, Cetyl Alcohol, Chlorphenesin, Dioscorea Villosa (Wild Yam) Root Extract, Disodium EDTA, Ethylhexyl Palmitate, Glycerin, Glycolic Acid, Palmitic Acid, Phenoxyethanol, Phenyl Trimethicone, Purified Water, Quillaja Saponaria Bark Extract, Smilax Aristolochiifolia Root Extract, Sodium Hydroxide, Sodium Lauryl Sulfate, Sodium Metabisulfite, Sodium Sulfite, Stearyl Alcohol, Tocopheryl Acetate, Yucca Schidigera Root Extract.

CLINICAL PHARMACOLOGY

Topical application of hydroquinone produces a reversible depigmentation of the skin by inhibition of the enzymatic oxidation of tyrosine to 3,4-dihydroxyphenylalanine (DOPA) and suppression of other melanocyte metabolic processes. Exposure to sunlight or ultraviolet light will cause re-pigmentation of bleached areas, which may be prevented by the use of the sunscreen agents.

INDICATIONS AND USAGE

For the gradual bleaching of hyperpigmented skin conditions such as cholasma, melasma, freckles, senile lentigines, and other unwanted areas of melanin hyperpigmentation.

CONTRAINDICATIONS

Prior history of sensitivity or allergic reaction to hydroquinone or to any other ingredient in this product. The safety of topical hydroquinone use during pregnancy or in children (12 years and under) has not been established.

WARNINGS

Hydroquinone is a skin bleaching agent which may produce undesired effects if not used as directed. The physician should be familiar with the contents of this insert before prescribing or dispensing this product.

Contains sodium metabisulfite, a sulfite that may cause allergic-type reactions including anaphylactic symptoms and life-threatening or less severe asthmatic episodes in certain susceptible people. The overall prevalence of sulfite sensitivity in the general population is unknown and probably low. Sulfite sensitivity is seen more frequently in asthmatic than in non-asthmatic people.

Avoid unnecessary sun exposure, use an effective broad-spectrum sunscreen agent or protective clothing should be worn to cover bleached skin to prevent re-pigmentation from occurring.

Hydroquinone may produce exogenous ochronosis, a gradual blue-black darkening of the skin. If this condition occurs, discontinue treatment and consult your physician.

Avoid contact with eyes and mucous membranes. Keep out of reach of children. In case of accidental ingestion, call a physician or a poison control center immediately.

PRECAUTIONS

Test for skin sensitivity before using by applying a small amount to an unbroken patch of skin; check within 24 hours. Minor redness is not a contraindication, but where there is itching or vesicle formation or excessive inflammatory response, further treatment is not advised. Close patient supervision is recommended.

Drug Interactions

Patients are cautioned on concomitant use of medications that are known to be photosensitizing.

Carcinogenesis, Mutagenesis, Impairment of Fertility

Studies of hydroquinone in animals have demonstrated some evidence of carcinogenicity. The carcinogenic potential of hydroquinone in humans is unknown.

Pregnancy Category C

Animal reproduction studies have not been conducted with topical hydroquinone. It is also not known whether topical hydroquinone can cause fetal harm when administered to a pregnant woman or can affect reproduction capacity. Topical hydroquinone should be given to a pregnant woman only if clearly needed.

Nursing Mothers

It is not known whether this drug is excreted in human milk. Because many drugs are excreted in human milk, caution should be exercised when topical hydroquinone is administered to a nursing woman.

Pediatric Use

Safety and effectiveness for pediatric patients below the age of 12 years have not been established.

Adverse Reactions

The following reactions have been reported: dryness and fissuring of paranasal and infraorbital areas, erythema, and stinging. Occasional hypersensitivity (localized contact dermatitis) may develop. If this occurs, the medication should be discontinued, and the physician notified immediately.

Overdosage

There have been no system reactions reported from the use of topical hydroquinone. However, treatment should be limited to relatively small areas of the body at one time, since some patients experience a transient skin reddening and a mild burning sensation which does not preclude treatment.

DRUG DOSAGE AND ADMINISTRATION

A thin application of Pigment Control + Blending Creme should be applied to the affected area twice daily or as directed by a physician. Consult product label for instructions on whether to rub in or not. There is no recommendation for children under 12 years of age except under the advice and supervision of a physician.

HOW SUPPLIED

Pigment Control + Blending Creme (Hydroquinone USP, 4%) is available as follows:

2.7 Fl. Oz. (80 mL) Bottle / NDC 42851-036-80

1.0 Fl. Oz (30 mL) Bottle / NDC 42851-036-30

STORAGE

Store at controlled room temperature: 15°-30°C (59°-86°F)

PRINCIPAL DISPLAY PANEL - Kit Carton

ZO®SKIN HEALTH
BY ZEIN OBAGI MD

PIGMENT CONTROL PROGRAM
+ HYDROQUINONE

NDC 42851-184-60

GENTLE CLEANSER 60 mL / 2 Fl. Oz.

EXFOLIATING POLISH Net Wt. 16.2 g / 0.57 Oz.

COMPLEXION RENEWAL PADS 30 Pads

PIGMENT CONTROL CRÈME 30 mL / 1.0 Fl. Oz.

DAILY POWER DEFENSE 30 mL / 1 Fl. Oz.

PIGMENT CONTROL + BLENDING CREME 30 mL / 1 Fl. Oz.